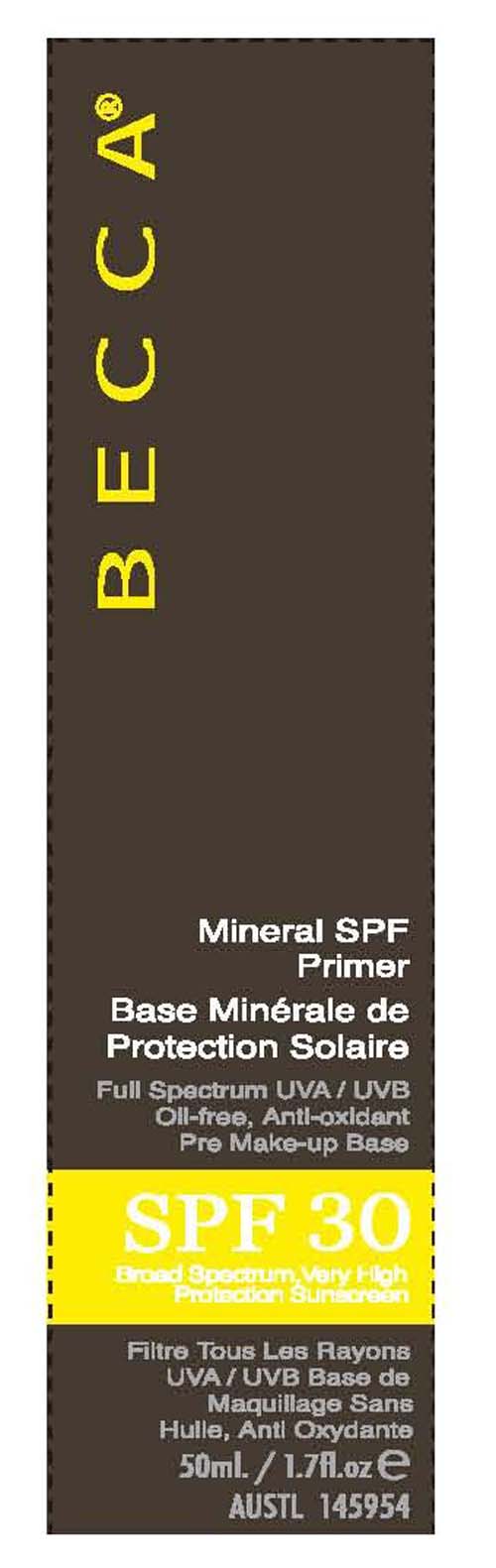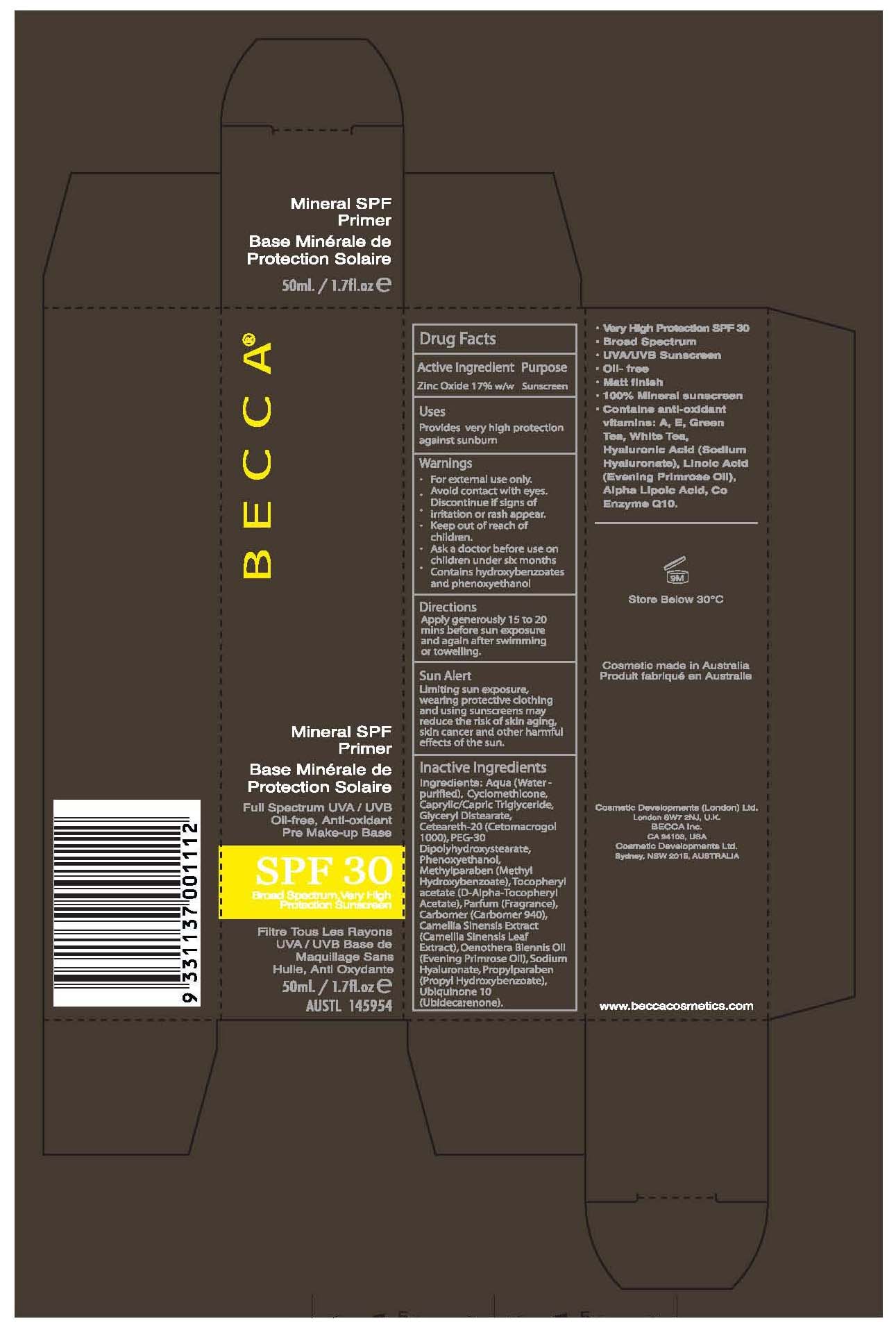 DRUG LABEL: Becca
NDC: 51147-5010 | Form: CREAM
Manufacturer: Becca, Inc.
Category: otc | Type: HUMAN OTC DRUG LABEL
Date: 20110414

ACTIVE INGREDIENTS: ZINC OXIDE 17 mL/100 mL
INACTIVE INGREDIENTS: CYCLOMETHICONE; MEDIUM-CHAIN TRIGLYCERIDES; GLYCERYL DISTEARATE; POLYOXYL 20 CETOSTEARYL ETHER; PEG-30 DIPOLYHYDROXYSTEARATE; PHENOXYETHANOL; METHYLPARABEN; .ALPHA.-TOCOPHEROL ACETATE, D-; CARBOMER HOMOPOLYMER TYPE C; GREEN TEA LEAF; EVENING PRIMROSE OIL; HYALURONATE SODIUM; PROPYLPARABEN; UBIDECARENONE; WATER

Mineral SPF30 Primer

Active Ingredients Purpose

Zinc Oxide 17% Sunscreen

PURPOSE

provides very high protection against sunburn

Keep out of reach of children

INDICATIONS AND USAGE

For external use only.

WARNINGS

Avoid contact with eyes.
-Discontinue if signs of irritation or rash appear
-Keep out of reach of children
-Ask a doctor before use on children under six months
-Contains hydroxybenzoates and phenoxyethanol

DOSAGE AND ADMINISTRATION

-Apply generously 15 to 20 minutes before sun exposure and again after swimming or toweling

INACTIVE INGREDIENT

Inactive Ingredients: Aqua (water-purified), Cyclomethicone, Caprylic/Capric Triglyceride, Glyceryl Distearate, Ceteareth-20 (Cetomacrogol 1000), PEG-30 Dipolyhydroxystearate, Phenoxyethanol, Methylparaben (Methyl Hydroxybenzoate), Tocopheryl acetate (D-Alpha-Tocopheryl Acetate), Parfum (Fragrance), Carbomer (Carbomer 940), Camellia Sinensis Extract (Camellia Sinensis Leaf Extract, Oenothera Biennis Oil (Evening Primrose Oil), Sodium Hyaluronate, Propylparaben (Propyl Hydroxybenzoate), Ubiquinone 10 (Ubidecarenone).

PACKAGE LABEL

Becca
Mineral SPF Primer
SPF 30
50 ml. / 1.7 fl.oz